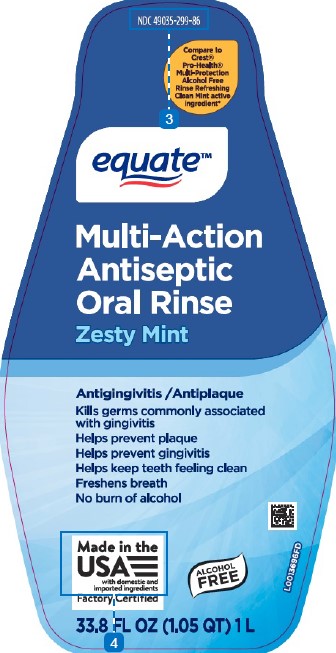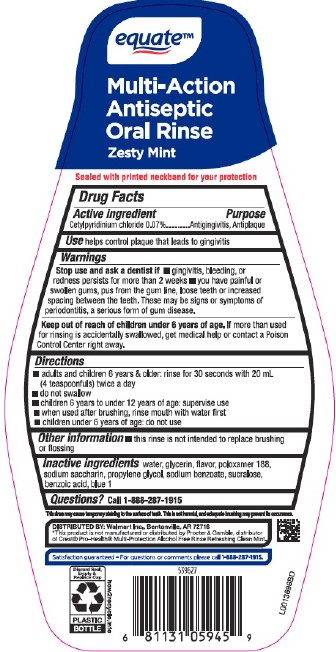 DRUG LABEL: Antiseptic
NDC: 49035-299 | Form: RINSE
Manufacturer: Walmart Inc.
Category: otc | Type: HUMAN OTC DRUG LABEL
Date: 20260227

ACTIVE INGREDIENTS: CETYLPYRIDINIUM CHLORIDE 0.7 mg/1 mL
INACTIVE INGREDIENTS: WATER; GLYCERIN; POLOXAMER 188; SACCHARIN SODIUM; PROPYLENE GLYCOL; SODIUM BENZOATE; SUCRALOSE; BENZOIC ACID; FD&C BLUE NO. 1

Equate 299.005/299AL
Multi Action Alcohol Free Antiseptic Rinse w/CPC

Claims

equate™

Multi-Action Antiseptic Oral Rinse

Zesty Mint

Tamper Evident Statement

Sealed with printed neckband for your protection

Active ingredient

Cetylpyridinium chloride 0.07%

Purpose

Antigingivitis, Antiplaque

Use

helps control plaque that leads to gingivitis

Warnings

for this product only

Stop use and ask a dentist if

- gingivitis, bleeding, or redness persists for more than 2 weeks
- you have painful or swollen gums, pus from the gum line, loose teeth or increased spacing between the teeth. These may be signs or symptoms of periodontitis, a serious form of gum disease.

Keep out of reach of children under 6 years of age.

If more than used for rinsing is accidentally swallowed, get medical help or contact a Poison Control Center right away.

Directions

- adults and children 6 years & older: rinse for 30 seconds with 20 mL (4 teaspoonfuls) twice a day
- do not swallow
- children 6 years to under 12 years of age: supervise use
- when used after brushing, rinse mouth with water first
- children under 6 yearsof age: do not use

Other information

- this rinse is not intended to replace brushing or flossing

Inactive ingredients

water, glycerin, flavor, poloxamer 188, sodium saccharin, propylene glycol, sodium benzoate, sucralose, benzoic acid, blue 1

Questions?

Call 1-888-287-1915

Adverse reaction

Distributed by Walmart Inc., Bentonville AR, 72716

Statisfaction guaranteed - For questions or comments please call 1-888-287-1915.

Discard Seal, Empty & Replace Cap

PLASTIC BOTTLE

how2recycle.info

Disclaimers

This rinse may cause temporary staining to the surface of teeth. This is not harmful, and adequate brushing may prevent its occurrence.

*This product is not manufactured or distributed by Procter & Gamble distributor of Crest®Pro-Health®Multi-Protection Alcohol Free Rinse Refreshing Clean Mint.

Principal display panel

NDC 49035-299-86

Compare to Crest® Pro-Health® Multi-Protection Alcohol Free Rinse Refreshing Clean Mint active ingredient*

equate™

Multi-Action Antiseptic Oral Rinse

Zesty Mint

Antigingivitis/Antiplaque

Kills germs commonly associated with gingivitis

Helps prevent plaque

Helps prevent gingivitis

Helps keep teeth feeling clean

Freshens breath

No burn of alcohol

ALCOHOL FREE

Made in the USA with domestic and imported ingredients

Factory Certified

33.8 FL OZ (1.05 QT) 1 L